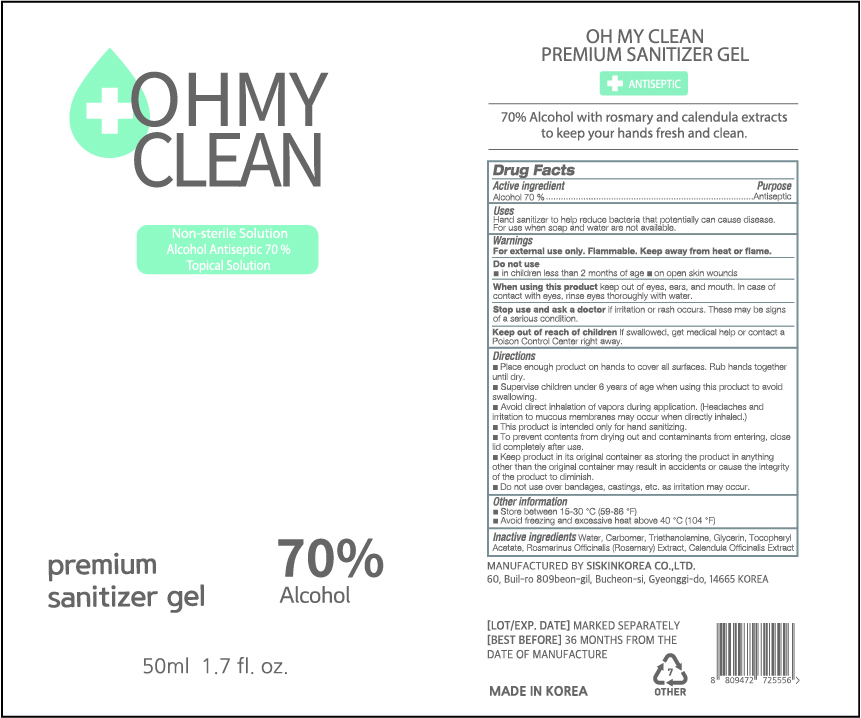 DRUG LABEL: OH MY CLEAN PREMIUM SANITIZER Gel
NDC: 74514-5070 | Form: GEL
Manufacturer: SISKINKOREA CO.,LTD.
Category: otc | Type: HUMAN OTC DRUG LABEL
Date: 20200514

ACTIVE INGREDIENTS: ALCOHOL 35 mL/50 mL
INACTIVE INGREDIENTS: TROLAMINE; GLYCERIN; .ALPHA.-TOCOPHEROL ACETATE; CALENDULA OFFICINALIS WHOLE; WATER; ROSEMARY; CARBOMER HOMOPOLYMER, UNSPECIFIED TYPE

Packaging change 50ml_70%_gel_OH MY CLEAN PREMIUM SANITIZER GEL [74514-0057-1]-> 74514-5070-1